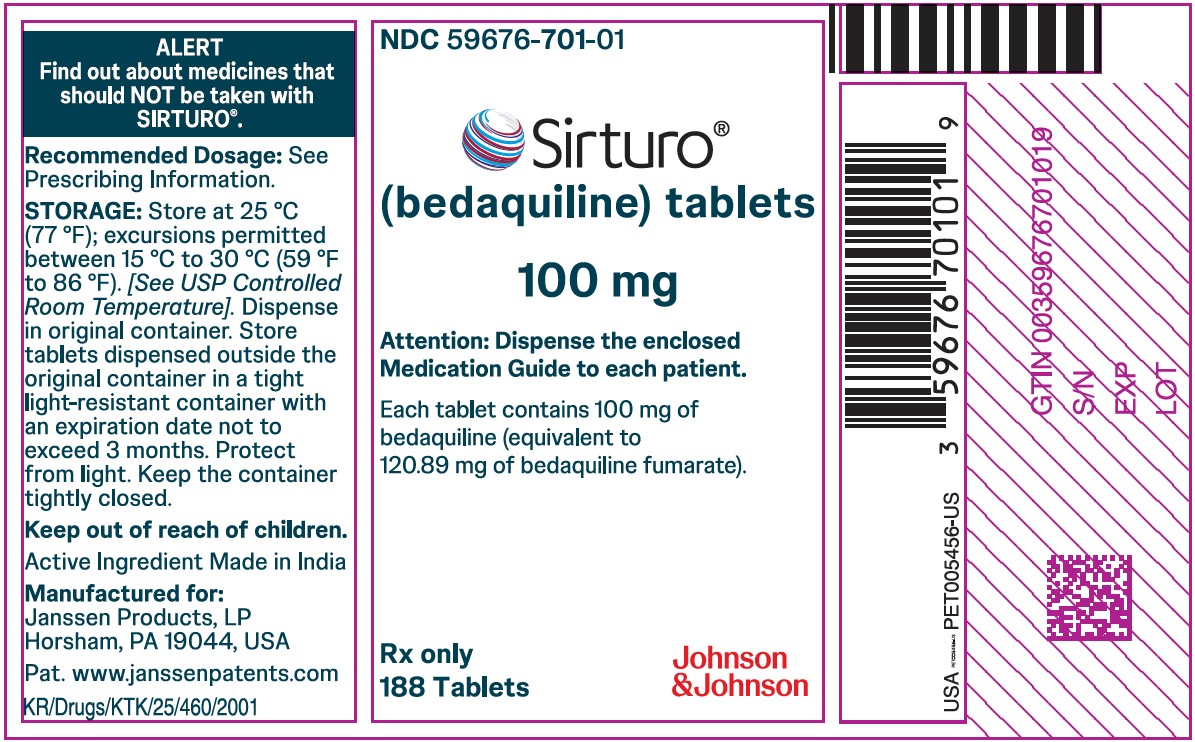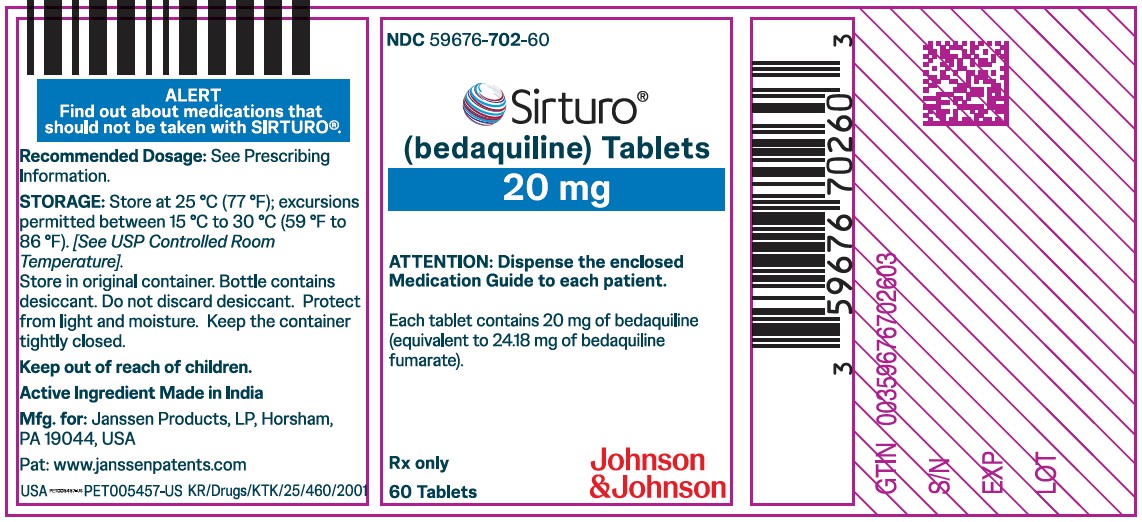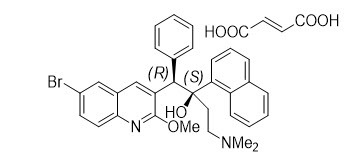 DRUG LABEL: SIRTURO
NDC: 59676-701 | Form: TABLET
Manufacturer: Janssen Products, LP
Category: prescription | Type: HUMAN PRESCRIPTION DRUG LABEL
Date: 20251017

ACTIVE INGREDIENTS: BEDAQUILINE FUMARATE 100 mg/1 1
INACTIVE INGREDIENTS: SILICON DIOXIDE; CROSCARMELLOSE SODIUM; HYPROMELLOSE 2910 (15 MPA.S); LACTOSE MONOHYDRATE; MAGNESIUM STEARATE; MICROCRYSTALLINE CELLULOSE; POLYSORBATE 20; WATER; STARCH, CORN

HIGHLIGHTS OF PRESCRIBING INFORMATION

These highlights do not include all the information needed to use SIRTURO safely and effectively. See full prescribing information for SIRTURO.
SIRTURO®(bedaquiline) tablets, for oral use
Initial U.S. Approval: 2012

WARNING: QTc PROLONGATION

See full prescribing information for complete boxed warning.

QTc Prolongation

QTc prolongation can occur with SIRTURO. Use with drugs that prolong the QTc interval may cause additive QTc prolongation. Monitor ECGs. Discontinue SIRTURO if significant ventricular arrhythmia or QTc interval greater than 500 ms develops. (5.1)

RECENT MAJOR CHANGES

Indications and Usage (1) | 7/2025
Dosage and Administration (2.4) | 7/2025

1 INDICATIONS AND USAGE

SIRTURO is a diarylquinoline antimycobacterial drug indicated as part of combination therapy in adult and pediatric patients (2 years and older and weighing at least 8 kg) with pulmonary tuberculosis (TB) due to Mycobacterium tuberculosis resistant to at least rifampin and isoniazid. (1)

Limitations of Use:

- Do not use SIRTURO for the treatment of latent, extra-pulmonary or drug-sensitive TB or for the treatment of infections caused by non-tuberculous mycobacteria. (1)

2 DOSAGE AND ADMINISTRATION

- Administer SIRTURO by directly observed therapy (DOT). (2.1)
- Emphasize need for compliance with full course of therapy. (2.1)
- Prior to administration, obtain ECG, liver enzymes and electrolytes. Obtain susceptibility information for the background regimen against Mycobacterium tuberculosis isolate if possible. (2.2)
- Only use SIRTURO in combination with at least 3 other drugs to which the patient's TB isolate has been shown to be susceptible in vitro. If in vitro testing results are unavailable, may initiate SIRTURO in combination with at least 4 other drugs to which patient's TB isolate is likely to be susceptible. (2.1)
- Recommended dosage in adult patients: 400 mg (4 of the 100 mg tablets OR 20 of the 20 mg tablets) once daily for 2 weeks followed by 200 mg (2 of the 100 mg tablets OR 10 of the 20 mg tablets) 3 times per week (with at least 48 hours between doses) for 22 weeks. (2.3)
- Recommended dosage in pediatric patients (2 years and older and weighing at least 8 kg) is based on body weight. (2.4)
- Take SIRTURO tablets with food. (2.6)
- See full prescribing information for the different methods of administration of SIRTURO 20 mg tablet and administration of the 100 mg tablet.

3 DOSAGE FORMS AND STRENGTHS

- Tablets: 20 mg, functionally scored (3)
- Tablets: 100 mg (3)

4 CONTRAINDICATIONS

None. (4)

5 WARNINGS AND PRECAUTIONS

- A mortality imbalance was seen in clinical trials in SIRTURO-treated patients with pulmonary TB due to Mycobacterium tuberculosis resistant to at least rifampin. (5.2)
- Hepatotoxicity may occur with use of SIRTURO. Monitor liver-related laboratory tests. Discontinue SIRTURO if evidence of liver injury occurs. (5.4)

6 ADVERSE REACTIONS

- The most common adverse reactions reported in 10% or more adult patients treated with SIRTURO in Study 1 were nausea, arthralgia, headache, hemoptysis and chest pain. (6.1)
- The most common adverse reactions reported in 10% or more adult patients treated with SIRTURO (40-week arm) in Study 4 were QTc prolongation, nausea, vomiting, arthralgia, transaminases increased, abdominal pain, pruritus, dizziness, headache, chest pain, rash, insomnia, dry skin, and palpitations. (6.1)
- The most common adverse reactions reported in 10% or more of pediatric patients (12 years to less than 18 years of age) treated with SIRTURO were arthralgia, nausea and abdominal pain. (6.1)
- The most common adverse reaction reported in 10% or more of pediatric patients (5 years to less than 12 years of age) treated with SIRTURO was elevation in liver enzymes. (6.1)
- The most common adverse reaction reported in 10% or more of pediatric patients (2 years to less than 5 years of age) treated with SIRTURO was vomiting. (6.1)

To report SUSPECTED ADVERSE REACTIONS, contact Janssen Therapeutics, Division of Janssen Products, LP at 1-800-JANSSEN (1-800-526-7736) or FDA at 1-800-FDA-1088 or www.fda.gov/medwatch.

7 DRUG INTERACTIONS

- Avoid use of strong and moderate CYP3A4 inducers with SIRTURO. (7.1)
- Closely monitor patient safety (e.g., liver function) when SIRTURO is coadministered with CYP3A4 inhibitors. (5.4, 7.1)

8 USE IN SPECIFIC POPULATIONS

- Lactation: Breastfeeding is not recommended unless infant formula is not available. If an infant is exposed to bedaquiline through breast milk, monitor for signs of bedaquiline-related adverse reactions, such as hepatotoxicity. (6, 8.2)
- Pediatrics: The safety and effectiveness of SIRTURO in pediatric patients less than 2 years of age and/or weighing less than 8 kg have not been established. (8.4)
- Use with caution in patients with severe hepatic impairment and only when the benefits outweigh the risks. Monitor for SIRTURO-related adverse reactions. (8.6)
- Use with caution in patients with severe renal impairment. (8.7)

FULL PRESCRIBING INFORMATION

WARNING: QTc PROLONGATION

QTc prolongation can occur with SIRTURO. Use with drugs that prolong the QTc interval may cause additive QTc prolongation. Monitor ECGs. Discontinue SIRTURO if significant ventricular arrhythmia or QTc interval greater than 500 ms develops [see Warnings and Precautions (5.1)] .

1 INDICATIONS AND USAGE

SIRTURO is a diarylquinoline antimycobacterial drug indicated as part of combination therapy in the treatment of adult and pediatric patients (2 years and older and weighing at least 8 kg) with pulmonary tuberculosis (TB) due to Mycobacterium tuberculosis resistant to at least rifampin and isoniazid.

Limitations of Use

- Do not use SIRTURO for the treatment of:
  - Latent infection due to Mycobacterium tuberculosis (M. tuberculosis)
  - Drug-sensitive pulmonary TB
  - Extra-pulmonary TB
  - Infections caused by non-tuberculous mycobacteria

2 DOSAGE AND ADMINISTRATION

2.1 Important Administration Instructions

- Administer SIRTURO by directly observed therapy (DOT).
- Only use SIRTURO in combination with at least three other drugs to which the patient's TB isolate has been shown to be susceptible in vitro. If in vitro testing results are unavailable, SIRTURO treatment may be initiated in combination with at least four other drugs to which the patient's TB isolate is likely to be susceptible. Refer to the prescribing information of the drugs used in combination with SIRTURO for further information.
- SIRTURO (20 mg and 100 mg) must be taken with food.
- SIRTURO 20 mg are functionally scored tablets which can be split at the scored lines into two equal halves of 10 mg each to provide doses less than 20 mg [see Dosage and Administration (2.6)].
- As an alternative method of administration, SIRTURO 20 mg tablets can be dispersed in water and administered or dispersed in water and further mixed with a beverage or soft food, or crushed and mixed with soft food, or administered through a feeding tube [see Dosage and Administration (2.6)].
- Emphasize the need for compliance with the full course of therapy.

2.2 Required Testing Prior to Administration

Prior to treatment with SIRTURO, obtain the following:

- Susceptibility information for the background regimen against M. tuberculosis isolate if possible [see Dosage and Administration (2.1)]
- ECG [see Warnings and Precautions (5.1)]
- Serum potassium, calcium, and magnesium concentrations [see Warnings and Precautions (5.1)]
- Liver enzymes [see Warnings and Precautions (5.4)]

2.3 Recommended Dosage in Adult Patients

The recommended dosage of SIRTURO in adult patients is:

Table 1: Recommended Dosage of SIRTURO in Adult Patients
Dosage Recommendation
Weeks 1 and 2 | Weeks 3 to 24 [At least 48 hours between doses]
400 mg (4 of the 100 mg tablets OR 20 of the 20 mg tablets) orally once daily | 200 mg (2 of the 100 mg tablets OR 10 of the 20 mg tablets) orally three times per week

Recommended dosage in pediatric patients is described in Table 2 below [see Dosage and Administration (2.4)].

Administer SIRTURO tablets with food. The total duration of treatment with SIRTURO in adults is 24 weeks. When treatment with SIRTURO is considered necessary beyond 24 weeks, treatment may be continued at a dose of 200 mg three times per week [see Clinical Studies (14.1)] .

2.4 Recommended Dosage in Pediatric Patients (2 years and older and weighing at least 8 kg)

The recommended dosage of SIRTURO in pediatric patients (2 years and older and weighing at least 8 kg) is based on body weight and shown in Table 2:

Table 2: Recommended Dosage of SIRTURO in Pediatric Patients (2 years and older and weighing at least 8 kg)
Body Weight | Dosage Recommendation
Body Weight | Weeks 1 and 2 | Weeks 3 to 24 [At least 48 hours between doses]
8 kg to less than 10 kg | 80 mg (4 of the 20 mg tablets) orally once daily | 40 mg (2 of the 20 mg tablets) orally three times per week
10 kg to less than 15 kg | 120 mg (6 of the 20 mg tablets) orally once daily | 60 mg (3 of the 20 mg tablets) orally three times per week
15 kg to less than 30 kg | 200 mg (2 of the 100 mg tablets OR 10 of the 20 mg tablets) orally once daily | 100 mg (1 of the 100 mg tablets OR 5 of the 20 mg tablets) orally three times per week
Greater than or equal to 30 kg | 400 mg (4 of the 100 mg tablets OR 20 of the 20 mg tablets) orally once daily | 200 mg (2 of the 100 mg tablets OR 10 of the 20 mg tablets) orally three times per week

Administer SIRTURO tablets with food. The total duration of treatment with SIRTURO is 24 weeks. When treatment with SIRTURO is considered necessary beyond 24 weeks in patients 16 years and older, and weighing at least 30 kg, treatment may be continued at a dose of 200 mg three times per week [see Clinical Studies (14.1)] .

2.5 Missed Dose

If a dose is missed during the first 2 weeks of treatment, do not administer the missed dose (skip the dose and then continue the daily dosing regimen). From Week 3 onwards, if a dose is missed, administer the missed dose as soon as possible, and then resume the 3 times a week dosing regimen. The total dose of SIRTURO during a 7-day period should not exceed the recommended weekly dose (with at least 24 hours between each intake).

2.6 Method of Administration

There is one method of administration of SIRTURO 100 mg tablet and four different methods of administration of SIRTURO 20 mg tablet as follows, each of which must be taken with food:

- For SIRTURO 100 mg tablet, administer the tablet whole with water. Take with food.
- For SIRTURO 20 mg tablet, the four different methods of administration are outlined below. Each administration method requires SIRTURO to be taken with food in addition to any soft food or beverage used to administer SIRTURO by the different methods for patients who cannot swallow intact SIRTURO 20 mg tablets.

Methods of Administration of SIRTURO 20 mg Tablet

Administration of 20 mg Tablets to Patients Who Can Swallow Intact Tablets:

Administer SIRTURO 20 mg tablet whole or split in half along the functional score line into two equal halves of 10 mg each. Administer SIRTURO 20 mg tablet with water. Take with food.

Administration of 20 mg Tablets to Patients Who Cannot Swallow Intact Tablets:

Dispersed in Water and Mixed with Beverage or Soft Food

For patients who have difficulty swallowing intact tablets, SIRTURO 20 mg tablet can be dispersed in water prior to administration with food. If needed to aid with administration, the dispersed mixture in water can be further mixed with a beverage (e.g., water, milk products, apple juice, orange juice, cranberry juice or carbonated beverage) or soft food (e.g., yogurt, apple sauce, mashed banana or porridge) as follows:

- Disperse tablets in water (maximum of 5 tablets in 5 mL of water) in a drinking cup.
- Mix the contents of the cup well until the tablets are completely dispersed and then orally administer the contents of the cup immediately with food. If needed to aid with oral administration, the dispersed mixture in water can be further mixed with at least 5 mL of beverage or 1 teaspoonful of soft food and then orally administer the contents of the cup immediately.
- If the total dose requires more than 5 tablets, repeat the above preparation steps with the appropriate number of additional tablets until the desired dose is reached.
- Ensure no tablet residue is left in the cup, rinse with beverage or add more soft food and orally administer the contents of the cup immediately.
- Take with food in addition to any beverage or soft food used to aid in administration.

Crushed and Mixed with Soft Food

SIRTURO 20 mg tablet can be crushed and mixed with soft food (e.g., yogurt, apple sauce, mashed banana or porridge) immediately prior to use and administered orally. To ensure no tablet residue is left in the container, add more soft food and administer the contents immediately. Take with food in addition to any beverage or soft food used to aid in administration.

Administration Through a Feeding Tube

SIRTURO 20 mg tablet can be administered through a feeding tube (8 French or greater) as follows:

- Disperse 5 tablets or less in 50 mL of non-carbonated water and mix well. Mixture should be white to almost white with visible particles expected.
- Administer through the feeding tube immediately.
- Repeat with additional tablets until desired dose is reached.
- Rinse and flush with 25 mL of additional water to ensure no tablet residue is left in materials used for preparation or the feeding tube.
- Administer with food.

3 DOSAGE FORMS AND STRENGTHS

- SIRTURO 20 mg tablet: uncoated, white to almost white oblong functionally scored tablet, with a score line on both sides, debossed with "2" and "0" on one side and plain on the other side.
- SIRTURO 100 mg tablet: uncoated, white to almost white round biconvex tablet with debossing of "T" over "207" on one side and "100" on the other side.

4 CONTRAINDICATIONS

None.

5 WARNINGS AND PRECAUTIONS

5.1 QTc Prolongation

SIRTURO prolongs the QTc interval [see Clinical Pharmacology (12.2)] . Use with drugs that prolong the QTc interval may cause additive QTc prolongation [see Adverse Reactions (6)] . In Study 4, where SIRTURO was administered with the QTc prolonging drugs clofazimine and levofloxacin, 5% of patients in the 40-week SIRTURO treatment group experienced a QTc ≥500 ms and 43% of patients experienced an increase in QTc ≥60 ms over baseline. Of the clofazimine- and levofloxacin-treated patients in the 40-week control arm, 7% of patients experienced a QTc ≥500 ms and 39% experienced an increase in QTc ≥60 ms over baseline.

Obtain an ECG before initiation of treatment, 2 weeks after initiation, during treatment, as clinically indicated and at the expected time of maximum increase in the QTc interval of the concomitantly administered QTc prolonging drugs (as applicable). Obtain electrolytes at baseline and during treatment and correct electrolytes as clinically indicated.

The following may increase the risk for QTc prolongation when patients are taking SIRTURO:

- use with other QTc prolonging drugs
- a history of Torsade de Pointes
- a history of congenital long QTc syndrome
- a history of or ongoing hypothyroidism
- a history of or ongoing bradyarrhythmias
- a history of uncompensated heart failure
- serum calcium, magnesium, or potassium levels below the lower limits of normal

Discontinue SIRTURO if the patient develops:

- Clinically significant ventricular arrhythmia
- A QTc interval of greater than 500 ms (confirmed by repeat ECG)

If syncope occurs, obtain an ECG to detect QTc prolongation.

5.2 Mortality Imbalance in Clinical Trials

An increased risk of death was seen in the SIRTURO treatment group (9/79, 11.4%) compared to the placebo treatment group (2/81, 2.5%) in one placebo-controlled trial in adults (Study 1; based on the 120 week visit window). One death occurred during the 24 weeks of administration of SIRTURO. The imbalance in deaths is unexplained. No discernible pattern between death and sputum culture conversion, relapse, sensitivity to other drugs used to treat tuberculosis, HIV status, or severity of disease could be observed. In a subsequent active-controlled trial in adults (Study 4), deaths by Week 132 occurred in 11/211 (5.2%) patients in the 40-week SIRTURO treatment group, 8/202 (4%) patients in the active-control treatment group including four of 29 patients who received SIRTURO as part of a salvage treatment, and 2/143 (1.4%) patients in the 28-week SIRTURO treatment group [see Adverse Reactions (6.1)] .

5.3 Risk of Development of Resistance to Bedaquiline

A potential for development of resistance to bedaquiline in M. tuberculosis exists [see Microbiology (12.4)]. Bedaquiline must only be used in an appropriate combination regimen for the treatment of pulmonary TB due to M. tuberculosis resistant to at least rifampin and isoniazid, to reduce the risk of development of resistance to bedaquiline [see Indications and Usage (1)] .

5.4 Hepatotoxicity

In clinical trials, more hepatic-related adverse reactions were reported in adults with the use of SIRTURO plus other drugs used to treat TB compared to other drugs used to treat TB without the addition of SIRTURO. Alcohol and other hepatotoxic drugs should be avoided while on SIRTURO, especially in patients with impaired hepatic function. Hepatic-related adverse reactions have also been reported in pediatric patients 5 years of age and older [see Adverse Reactions (6.1)] .

Monitor symptoms (such as fatigue, anorexia, nausea, jaundice, dark urine, liver tenderness and hepatomegaly) and laboratory tests (ALT, AST, alkaline phosphatase, and bilirubin) at baseline, monthly while on treatment, and as needed. Test for viral hepatitis and discontinue other hepatotoxic medications if evidence of new or worsening liver dysfunction occurs. Discontinue SIRTURO if:

- transaminase elevations are accompanied by total bilirubin elevation greater than two times the upper limit of normal
- transaminase elevations are greater than eight times the upper limit of normal
- transaminase elevations are greater than five times the upper limit of normal and persist beyond two weeks

5.5 Drug Interactions

CYP3A4 Inducers

Coadministration of SIRTURO with a moderate or strong CYP3A4 inducer decreases the systemic exposure of bedaquiline and may reduce the therapeutic effect of SIRTURO. Avoid coadministration of SIRTURO with moderate or strong CYP3A4 inducers, such as efavirenz and rifamycins (i.e., rifampin, rifapentine and rifabutin) [see Drug Interactions (7.1)] .

CYP3A4 Inhibitors

Coadministration of SIRTURO with CYP3A4 inhibitors increases the systemic exposure of bedaquiline, which may increase the risk of adverse reactions. Closely monitor patient safety (e.g., liver function) when SIRTURO is coadministered with CYP3A4 inhibitors [see Drug Interactions (7.1)] .

6 ADVERSE REACTIONS

The following serious adverse reactions are discussed elsewhere in the labeling:

- QTc Prolongation [see Warnings and Precautions (5.1)and Clinical Pharmacology (12.2)]
- Mortality Imbalance in Clinical Trials [see Warnings and Precautions (5.2)]
- Hepatotoxicity [see Warnings and Precautions (5.4)]
- Drug Interactions [see Warnings and Precautions (5.5)]

6.1 Clinical Studies Experience

Because clinical studies are conducted under widely varying conditions, adverse reaction rates observed in the clinical studies of a drug cannot be directly compared to the rates in the clinical studies of another drug and may not reflect the rates observed in clinical practice. Refer to the prescribing information of the drugs used in combination with SIRTURO for their respective adverse reactions.

Clinical Studies Experience in Adults

Adverse reactions for SIRTURO were identified from safety data from 335 patients who received SIRTURO for eight weeks (Study 2) and 24 weeks (Studies 1 and 3), and 354 patients who received SIRTURO for 40 weeks or 28 weeks (Study 4). In these studies, patients received SIRTURO in combination with other antimycobacterial drugs.

Studies 1 and 2 were randomized, double-blind, placebo-controlled trials in newly diagnosed patients with pulmonary TB due to M. tuberculosis resistant to at least rifampin and isoniazid. Study 3 was an open-label, noncomparative study with SIRTURO administered as part of an individualized treatment regimen in previously treated patients with pulmonary TB due to M. tuberculosis resistant to at least rifampin and isoniazid, including patients resistant to second-line injectables and/or fluroquinolones.

In Study 1, 35% were Black, 17% were Hispanic, 13% were White, 9% were Asian, and 26% were of another race. Eight of 79 (10%) patients in the SIRTURO group and 16 of 81 (20%) patients in the placebo treatment group were HIV infected. Seven (8.9%) SIRTURO-treated patients and six (7.4%) placebo-treated patients discontinued Study 1 because of an adverse reaction.

Study 4 was an open-label, randomized, active-controlled trial in patients with pulmonary TB due to M. tuberculosis resistant to at least rifampin that evaluated a 40-week arm of SIRTURO in combination with other oral antimycobacterial drugs compared with a 40-week active control arm that included an injectable antimycobacterial drug in combination with other oral antimycobacterial drugs. A 28-week arm including SIRTURO, an injectable and other antimycobacterial drugs, was also evaluated in the trial, but recruitment was stopped early due to changes in the standard of care. In the population treated in the two 40-week arms (N=413), the median age was 32.8 years, 61% were male, 46% were Asian, 36% were Black, 18% were White and 16% were HIV infected.

Common Adverse Reactions

Table 3 presents select adverse reactions that occurred more frequently in the SIRTURO arm than the placebo arm in Study 1. The most common adverse reactions reported in 10% or more patients treated with SIRTURO and occurred more frequently than the placebo arm were nausea, arthralgia, headache, hemoptysis and chest pain.

Table 3: Select Adverse Reactions from Study 1 that Occurred More Frequently than Placebo During Treatment with SIRTURO
Adverse Reactions | SIRTURO Treatment Group N=79 n (%) | Placebo Treatment Group N=81 n (%)
Nausea | 30 (38) | 26 (32)
Arthralgia | 26 (33) | 18 (22)
Headache | 22 (28) | 10 (12)
Hemoptysis | 14 (18) | 9 (11)
Chest Pain | 9 (11) | 6 (7)
Anorexia | 7 (9) | 3 (4)
Transaminases Increased [Terms represented by 'transaminases increased' included transaminases increased, AST increased, ALT increased, hepatic enzyme increased, and hepatic function abnormal.] | 7 (9) | 1 (1)
Rash | 6 (8) | 3 (4)
Blood Amylase Increased | 2 (3) | 1 (1)

No additional unique adverse reactions were identified from the uncontrolled Study 3.

Transaminase Elevations

In both Studies 1 and 2, transaminase elevations of at least 3 times the upper limit of normal developed more frequently in the SIRTURO treatment group (11/102 [10.8%] vs 6/105 [5.7%]) than in the placebo treatment group. In Study 3, 22/230 (9.6%) patients had alanine aminotransferase (ALT) or aspartate aminotransferase (AST) greater than or equal to 3 times the upper limit of normal during the overall treatment period.

In Study 4 during the treatment phase, transaminase elevations of at least 3 times the upper limit of normal developed in 45/211 (21%) in the 40-week SIRTURO treatment group, 45/202 (22%) in the 40-week active comparator group, and 23 /143 (16%) in the 28-week SIRTURO-containing group.

Table 4 presents select adverse reactions occurring in 5% or greater of patients receiving SIRTURO in combination with other antimycobacterial drugs in the 40-week SIRTURO arm in Study 4. The most common adverse reactions reported in 10% or more patients in the 40-week SIRTURO arm were QTc prolongation, nausea, vomiting, arthralgia, transaminases increased, abdominal pain, pruritus, dizziness, headache, chest pain, rash, insomnia, dry skin, and palpitations.

Table 4: Select Adverse Reactions Occurring in 5% or Greater of Patients Receiving the 40-Week SIRTURO Regimen in Study 4
Adverse Reactions | SIRTURO [40-week, bedaquiline, levofloxacin, clofazimine, ethambutol, and pyrazinamide, supplemented by high-dose isoniazid and prothionamide in the first 16 weeks (intensive phase).] N=211 n (%) | Active Control [40-week control treatment of moxifloxacin or levofloxacin, clofazimine, ethambutol, pyrazinamide, supplemented by injectable kanamycin, high dose isoniazid and prothionamide in the first 16 weeks (intensive phase).] , [Study 4 was not designed to evaluate meaningful comparisons of the incidence of adverse reactions in the SIRTURO and the active control treatment groups.] N=202 n (%)
QTc prolongation | 128 (61) | 113 (56)
Nausea | 114 (54) | 126 (62)
Vomiting | 112 (53) | 125 (62)
Arthralgia | 93 (44) | 67 (33)
Transaminases increased [Terms represented by 'transaminases increased' included AST increased, ALT increased, hepatic enzyme increased, hepatic function abnormal, hypertransaminasemia, and transaminases increased.] | 63 (30) | 59 (29)
Abdominal pain [Terms represented by 'abdominal pain' included abdominal pain, abdominal pain upper, abdominal pain lower, and abdominal tenderness.] | 60 (28) | 48 (24)
Pruritus [Terms represented by 'pruritus' included pruritus, pruritus generalized, and rash pruritic.] | 58 (27) | 44 (22)
Dizziness | 37 (18) | 42 (21)
Headache | 36 (17) | 36 (18)
Chest pain | 33 (16) | 24 (12)
Rash [Terms represented by 'rash' included rash, rash papular and rash maculopapular.] | 30 (14) | 17 (8)
Insomnia | 30 (14) | 19 (9)
Dry skin | 25 (12) | 16 (8)
Palpitations | 21 (10) | 13 (6)
Myalgia | 19 (9) | 6 (3)
Paresthesia | 16 (8) | 8 (4)
Diarrhea | 12 (6) | 17 (8)

In the 28-week SIRTURO-containing arm (N=143), in which SIRTURO was used in combination with other antimycobacterial drugs, the most common selected adverse reactions (greater than 10%) were QTc prolongation (56%), arthralgia (55%), nausea (43%), vomiting (29%), pruritus (25%), transaminases increased (21%), dizziness (21%), chest pain (17%), abdominal pain (17%), headache (16%), rash (12%), and hemoptysis (11%).

Mortality Imbalance in Clinical Studies

In Study 1, there was a statistically significant increased mortality risk by Week 120 in the SIRTURO treatment group compared to the placebo treatment group (9/79 (11.4%) versus 2/81 (2.5%), p-value=0.03, an exact 95% confidence interval of the difference [1.1%, 18.2%]). Five of the 9 SIRTURO deaths and the 2 placebo deaths were TB-related. One death occurred during the 24-week SIRTURO treatment period. The median time to death for the remaining eight patients in the SIRTURO treatment group was 329 days after last intake of SIRTURO. The imbalance in deaths is unexplained; no discernible pattern between death and sputum conversion, relapse, sensitivity to other drugs used to treat TB, HIV status, and severity of disease was observed.

In the open-label Study 3, 16/233 (6.9%) patients died. The most common cause of death as reported by the investigator was TB (nine patients).

In Study 4, patients originally assigned to non-SIRTURO containing regimens could receive SIRTURO as salvage when the original therapy was not tolerated or ineffective. At Week 132, deaths were observed in 11/211 (5.2%) patients in the 40-week SIRTURO arm versus 8/202 (4.0%) patients in the 40-week active control arm. For the 40-week SIRTURO arm, the most common cause of death was related to TB (five patients). In the 40-week active control arm, which included four of 29 patients who received SIRTURO as part of a salvage treatment, the most common cause of death was related to respiratory disease (e.g., TB, lobar pneumonia, respiratory distress in an HIV-positive patient). The adjusted difference in proportion of fatal adverse reactions between the 40-week SIRTURO arm and the 40-week active control arm was 1.2% [95% CI (-2.8%; 5.2%)]. In the 28-week SIRTURO arm at Week 132, 2/143 (1.4%) patients died; one of the two deaths was also related to TB. The overall mortality for patients treated with SIRTURO was 17/383 (4.4%).

Clinical Studies Experience in Pediatric Patients

The safety assessment of SIRTURO in pediatric patients is based on data from 45 pediatric patients in an ongoing, single-arm, open-label, multi-cohort trial.

Pediatric Patients (12 years to less than 18 years of age)

The first cohort was designed to enroll patients 12 years to less than 18 years of age (fifteen patients 14 years to less than 18 years of age were enrolled) with confirmed or probable pulmonary TB due to M. tuberculosis resistant to at least rifampin who received SIRTURO (400 mg once daily for the first 2 weeks and 200 mg 3 times per week for the following 22 weeks) in combination with a background regimen [see Clinical Studies (14.2)] .

The most common adverse reactions were arthralgia in 6/15 (40%) patients, nausea in 2/15 (13%) patients, and abdominal pain in 2/15 (13%) patients. Among the 15 patients, no deaths were reported during the study (Week 120 analysis). Observed laboratory abnormalities were comparable to those in adults.

Pediatric Patients (5 years to less than 12 years of age)

The second cohort was designed to enroll patients 5 years to less than 12 years of age (fifteen patients aged 5 years to less than 11 years of age were enrolled) with confirmed or probable pulmonary TB due to M. tuberculosis resistant to at least rifampin who received SIRTURO (200 mg once daily for the first 2 weeks and 100 mg 3 times per week for the following 22 weeks) in combination with a background regimen [see Clinical Studies (14.2)] .

The most common adverse reactions were related to elevations in liver enzymes (5/15, 33%), and led to discontinuation of SIRTURO in three patients. Elevations in liver enzymes were reversible upon discontinuation of SIRTURO and some of the background regimen drugs. Among these 15 pediatric patients, no deaths were reported during the study (Week 120 analysis).

Pediatric Patients (2 years to less than 5 years of age)

The third cohort enrolled 15 patients aged 2 years to less than 5 years of age with confirmed or probable pulmonary TB due to M. tuberculosis resistant to at least rifampin who received SIRTURO (80 to 120 mg once daily for the first 2 weeks and 40 to 60 mg 3 times per week for the following 22 weeks based on weight), in combination with a background regimen [see Clinical Studies (14.2)] .

The most common adverse reaction was vomiting in 3/15 (20%) patients. Among these 15 pediatric patients, no deaths were reported during treatment with SIRTURO (Week 24 analysis).

7 DRUG INTERACTIONS

7.1 Effect of Other Drugs on SIRTURO

Strong and Moderate CYP3A4 Inducers

Coadministration of SIRTURO with moderate or strong CYP3A4 inducers may decrease systemic exposure of bedaquiline. Avoid coadministration of SIRTURO with strong or moderate CYP3A4 inducers [see Clinical Pharmacology (12.3)] .

CYP3A4 Inhibitors

Coadministration of SIRTURO with CYP3A4 inhibitors increases the systemic exposure of bedaquiline which may increase the risk of adverse reactions. Closely monitor patient safety (e.g., liver function) when SIRTURO is coadministered with CYP3A4 inhibitors. No dose adjustment of SIRTURO is needed when coadministered with CYP3A4 inhibitors [see Clinical Pharmacology (12.3)] .

7.2 Other Antimicrobial Medications

No dose adjustment of isoniazid or pyrazinamide is required during coadministration with SIRTURO.

In a placebo-controlled clinical trial in adult patients, no major impact of coadministration of SIRTURO on the pharmacokinetics of ethambutol, kanamycin, pyrazinamide, ofloxacin or cycloserine was observed.

7.3 QTc Interval Prolonging Drugs

In clinical trials of adult patients, additional QTc interval prolongation was observed during combination treatment with SIRTURO and other QTc prolonging drugs.

In Study 3, concurrent use of clofazimine with SIRTURO resulted in QTc prolongation: mean increases in QTc were larger in the 17 adult patients who were taking clofazimine with bedaquiline at Week 24 (mean change from Day-1 of 32 ms) than in patients who were not taking clofazimine with bedaquiline at Week 24 (mean change from Day-1 of 12 ms). Monitor ECGs if SIRTURO is coadministered to patients receiving other drugs that prolong the QTc interval, and discontinue SIRTURO if there is evidence of serious ventricular arrhythmia or QTc interval greater than 500 ms [see Warnings and Precautions (5.1)and Clinical Pharmacology (12.2)] . ECG monitoring should be performed prior to initiation and at the expected time of maximum increase in the QTc interval of the concomitantly administered QTc prolonging drugs.

8 USE IN SPECIFIC POPULATIONS

8.1 Pregnancy

Risk Summary

Available data from published literature of SIRTURO use in pregnant women are insufficient to evaluate a drug-associated risk of major birth defects, miscarriage, or adverse maternal or fetal outcomes. There are risks associated with active TB during pregnancy (see Clinical Considerations) .

Reproduction studies performed in rats and rabbits have revealed no evidence of harm to the fetus due to oral administration of bedaquiline to pregnant rats and rabbits during organogenesis at exposures up to 6 times the clinical dose based on AUC comparisons (see Data) .

The estimated background risk of major birth defects and miscarriage for the indicated populations is unknown. All pregnancies have a background risk of birth defect, loss, or other adverse outcomes. In the U.S. general population, the estimated background risk of major birth defects and miscarriage in clinically recognized pregnancies is 2 to 4% and 15 to 20%, respectively.

Clinical Considerations

Disease-Associated Maternal and/or Embryo/Fetal Risk

Active TB in pregnancy is associated with adverse maternal and neonatal outcomes including maternal anemia, caesarean delivery, preterm birth, low birth weight, birth asphyxia, and perinatal infant death.

Data

Animal Data

Pregnant rats were treated with bedaquiline at 5, 15 and 45 mg/kg (approximately 0.7, 2 and 6 times the clinical dose based on AUC comparisons) during the period of organogenesis (gestational Days 6 to 17, inclusive). Pregnant rabbits were treated with bedaquiline at 10, 30 and 100 mg/kg (approximately 0.05, 0.2 and 1.5 times the clinical dose based on AUC comparisons) during the period of organogenesis (gestational Days 6 to 19, inclusive). No embryotoxic effects were found in rats or rabbits at dose exposures up to 6 times the clinical dose exposures based on AUC comparisons.

8.2 Lactation

Risk Summary

Data from a published clinical lactation study demonstrate higher bedaquiline concentrations in breast milk compared to maternal plasma, suggesting that bedaquiline accumulates in breast milk (see Data) . Data are insufficient to determine effects of the drug on the breastfed infants. No data are available on the effects of the drug on milk production. Because of the potential for serious adverse reactions in a breastfed infant, including hepatotoxicity, advise patients that breastfeeding is not recommended during treatment with SIRTURO and for 27.5 months (5 times the half-life) after the last dose unless infant formula is not available.

Clinical Considerations

If an infant is exposed to bedaquiline through breast milk, monitor for signs of bedaquiline-related adverse reactions, such as hepatotoxicity [see Adverse Reactions (6)].

Data

A clinical lactation study was conducted in two lactating women who were approximately 7 weeks' postpartum. Bedaquiline and M2, its active metabolite, levels were measured between approximately 27 and 48 hours after the last bedaquiline dose, and concentrations of bedaquiline and M2 ranged from 2.61 to 8.11 mg/L and 0.27 to 0.81 mg/L, respectively. The milk:plasma ratios for bedaquiline and M2 at 27 to 48 hours after the last dose of bedaquiline ranged from approximately 19 to 29 and 4 to 6, respectively.

8.4 Pediatric Use

The safety and effectiveness of SIRTURO have been established in pediatric patients 2 years and older weighing at least 8 kg. The use of SIRTURO in this pediatric population is supported by evidence from the study of SIRTURO in adults together with additional pharmacokinetic and safety data from the single-arm, open-label, multi-cohort trial that enrolled 45 pediatric patients 2 years to less than 18 years of age with confirmed or probable pulmonary TB caused by M. tuberculosis resistant to at least rifampin who were treated with SIRTURO for 24 weeks in combination with a background regimen [see Dosage and Administration (2.4), Adverse Reactions (6.1), Clinical Pharmacology (12.3)and Clinical Studies (14.2)] .

The safety, effectiveness and dosage of SIRTURO in pediatric patients less than 2 years of age and/or weighing less than 8 kg have not been established.

8.5 Geriatric Use

Clinical studies of SIRTURO did not include sufficient numbers of patients 65 years of age and older to determine whether they respond differently from younger adult patients [see Clinical Pharmacology (12.3)] .

8.6 Hepatic Impairment

The pharmacokinetics of bedaquiline were assessed after single-dose administration to adult patients with moderate hepatic impairment (Child-Pugh B) [see Clinical Pharmacology (12.3)] . Based on these results, no dose adjustment is necessary for SIRTURO in patients with mild or moderate hepatic impairment. SIRTURO has not been studied in patients with severe hepatic impairment and should be used with caution in these patients only when the benefits outweigh the risks. Clinical monitoring for SIRTURO-related adverse reactions is recommended [see Warnings and Precautions (5.4)] .

8.7 Renal Impairment

SIRTURO has mainly been studied in adult patients with normal renal function. Renal excretion of unchanged bedaquiline is not substantial (less than or equal to 0.001%). No dose adjustment is required in patients with mild or moderate renal impairment. In patients with severe renal impairment or end stage renal disease requiring hemodialysis or peritoneal dialysis, SIRTURO should be used with caution [see Clinical Pharmacology (12.3)] . Monitor adult and pediatric patients for adverse reactions of SIRTURO when administered to patients with severe renal impairment or end stage renal disease requiring hemodialysis or peritoneal dialysis.

10 OVERDOSAGE

There is no experience with the treatment of acute overdose with SIRTURO. Take general measures to support basic vital functions including monitoring of vital signs and ECG (QTc interval) in case of deliberate or accidental overdose. It is advisable to contact a poison control center to obtain the latest recommendations for the management of an overdose. Since bedaquiline is highly protein-bound, dialysis is not likely to significantly remove bedaquiline from plasma.

11 DESCRIPTION

SIRTURO® contains bedaquiline fumarate, a diarylquinoline antimycobacterial drug for oral administration. Each SIRTURO 20 mg tablet contains 20 mg of bedaquiline (equivalent to 24.18 mg of bedaquiline fumarate). Each SIRTURO 100 mg tablet contains 100 mg of bedaquiline (equivalent to 120.89 mg of bedaquiline fumarate).

Bedaquiline fumarate is a white to almost white powder and is practically insoluble in aqueous media. The chemical name of bedaquiline fumarate is (1 R, 2 S)-1-(6-bromo-2-methoxy-3-quinolinyl)-4-(dimethylamino)-2-(1-naphthalenyl)-1-phenyl-2-butanol compound with fumaric acid (1:1). It has a molecular formula of C32H31BrN2O2∙C4H4O4 and a molecular weight of 671.58 (555.50 + 116.07). The molecular structure of bedaquiline fumarate is the following:

SIRTURO 20 mg tablet contains the following inactive ingredients: colloidal silicon dioxide, crospovidone, hypromellose 2910 5 mPa.s, polysorbate 20, purified water (removed during processing), silicified microcrystalline cellulose and sodium stearyl fumarate.

SIRTURO 100 mg tablet contains the following inactive ingredients: colloidal silicon dioxide, corn starch, croscarmellose sodium, hypromellose 2910 15 mPa.s, lactose monohydrate, magnesium stearate, microcrystalline cellulose, polysorbate 20, purified water (removed during processing).

12 CLINICAL PHARMACOLOGY

12.1 Mechanism of Action

Bedaquiline is a diarylquinoline antimycobacterial drug [see Microbiology (12.4)] .

12.2 Pharmacodynamics

Bedaquiline has activity against M. tuberculosis. The major metabolite, M2 is not thought to contribute significantly to clinical efficacy given its lower average exposure (23% to 31%) in humans and lower antimycobacterial activity (3-fold to 6-fold lower) compared to the parent compound. However, M2 plasma concentrations are correlated with QTc prolongation.

Cardiac Electrophysiology

In Study 1, the largest mean increase in QTc during the 24 weeks of SIRTURO treatment was 16 ms compared to 6 ms with placebo treatment (at Week 18). After SIRTURO treatment ended, the QTc gradually decreased, and the mean value was similar to that in the placebo group by study Week 60.

In Study 4, the mean change from baseline in QTc for the SIRTURO-containing arm was 22 ms (95% CI: 19; 24) at Week 2 (i.e., the end of the 2-week SIRTURO loading period), and 8 ms (95% CI: 2; 13) in the levofloxacin-containing control arm subgroup.

In Study 4, the mean QTc increased from baseline over the first 12 weeks for both SIRTURO and the non-SIRTURO containing control arm, when a plateau was reached. The largest mean QTc increase from baseline was 35 ms (95% CI: 32 to 38 ms) for the SIRTURO-containing arm and 28 ms (95% CI: 21 to 34 ms) for the levofloxacin-containing control arm subgroup [see Warnings and Precautions (5.1)and Drug Interactions (7.3)].

12.3 Pharmacokinetics

Pharmacokinetics (PK) parameters

The pharmacokinetic properties of bedaquiline are summarized in Table 5 as mean (SD) in adult patients.

Table 5: Model-Derived Pharmacokinetic Parameters of Bedaquiline and M2 (mean [SD]) after Multiple Doses of SIRTURO at the Recommended Dosing Regimen
Pharmacokinetic Parameters | Bedaquiline
Absorption
Food effect | High fat meal (22 grams of fat, 558 total Kcal) increased Cmax and AUC by 2-fold. SIRTURO should be taken with food to enhance its oral bioavailability.
Tmax | Around 5 hours after single oral dose administration of SIRTURO
Cmax of bedaquiline | Week 2: 3060 (1124) ng/mL Week 24: 1838 (684) ng/mL Week 40: 1787 (666) ng/mL
Cmax of M2 | Week 2: 326 (135) ng/mL Week 24: 234 (85) ng/mL Week 40: 246 (103) ng/mL
Exposure
AUC168h of bedaquiline (AUC24h for Week 2) | Week 2: 41510 (15064) ng.h/mL Week 24: 163924 (55710) (ng.h/mL) Week 40: 168376 (74476) ng.h/mL
AUC168h of M2 (AUC24h for Week 2) | Week 2: 7267 (3029) ng.h/mL Week 24: 37255 (13998) ng.h/mL Week 40: 39540 (17220) ng.h/mL
Distribution
Percent bound to human plasma protein | greater than 99.9%.
apparent central volume of distribution | approximately 117 Liters.
Proportionality | Cmax and AUC increased proportionally up 700 mg (1.75 times the 400 mg loading dose).
Elimination | After reaching Cmax, bedaquiline concentrations decline tri-exponentially.
Apparent clearance of bedaquiline | 2.62 L/h
Apparent clearance of M2 | 4.95 L/h
Terminal half-life | ~ 5.5 months for both bedaquiline and Nmonodesmethyl metabolite (M2)
Metabolism | Metabolized to the M2 by CYP3A4; Relative exposure M2 versus bedaquiline: 23%~31%
Excretion
Major route of excretion | Fecal excretion is the major route of elimination
%Excreted unchanged in urine | less than or equal to 0.001% of the dose in clinical studies
SD=Standard Deviation

Specific Populations

Patients with Hepatic Impairment: After single-dose administration of 400 mg SIRTURO to 8 adult patients with moderate hepatic impairment (Child-Pugh B), mean exposure to bedaquiline and M2 (AUC672h) was approximately 20% lower compared to healthy adults. SIRTURO has not been studied in patients with severe hepatic impairment [see Warnings and Precautions (5.4)and Use in Specific Populations (8.6)].

Patients with Renal Impairment: SIRTURO has mainly been studied in adult patients with normal renal function. Renal excretion of unchanged bedaquiline is not substantial (less than or equal to 0.001%).

In a population pharmacokinetic analysis of adult TB patients treated with SIRTURO 200 mg three times per week, creatinine clearance was not found to influence the pharmacokinetic parameters of bedaquiline. It is therefore not expected that mild or moderate renal impairment will have a clinically relevant effect on the exposure to bedaquiline. However, in patients with severe renal impairment or end-stage renal disease requiring hemodialysis or peritoneal dialysis bedaquiline concentrations may be increased due to alteration of drug absorption, distribution, and metabolism secondary to renal dysfunction. As bedaquiline is highly bound to plasma proteins, it is unlikely that it will be significantly removed from plasma by hemodialysis or peritoneal dialysis [see Use in Specific Populations (8.7)] .

Male and Female Patients: In a population pharmacokinetic analysis of adult TB patients treated with SIRTURO no clinically relevant difference in exposure between men and women were observed.

Race or Ethnicity: In a population pharmacokinetic analysis of adult TB patients treated with SIRTURO, systemic exposure (AUC) to bedaquiline was found to be 34% lower in Black patients than in patients from other race categories. This lower bedaquiline exposure in Black patients was not associated with lower efficacy in clinical trials.

HIV Coinfection: Bedaquiline exposure in patients coinfected with HIV was similar to that of patients not infected with HIV.

Geriatric Patients: There are limited data on the use of SIRTURO in TB patients 65 years of age and older.

In a population pharmacokinetic analysis of adult TB patients treated with SIRTURO, age was not found to influence the pharmacokinetics of bedaquiline. In five patients 65 to 69 years of age, the systemic bedaquiline exposure was similar to that in other adults.

Pediatric Patients:

Pediatric patients 12 years to less than 18 years of age with TB due to M. tuberculosis resistant to at least rifampin

The pharmacokinetic parameters of bedaquiline in 15 pediatric patients (body weight at baseline: 38 to 75 kg) who received the same adult dosage regimen of SIRTURO (400 mg once daily for the first two weeks and 200 mg three times per week for the following 22 weeks) in combination with a background regimen were comparable to those in adults. There was no impact of body weight on bedaquiline pharmacokinetics in this cohort.

Pediatric patients 5 years to less than 12 years of age with TB due to M. tuberculosis resistant to at least rifampin

Fifteen pediatric patients (body weight at baseline: 14 to 36 kg) received SIRTURO (200 mg once daily for the first two weeks and 100 mg three times per week for the following 22 weeks) in combination with a background regimen. Of these 15 pediatric patients, complete pharmacokinetic data were obtained for 10 patients at the aforementioned dosage regimen of SIRTURO. In nine of these 10 pediatric patients who weighed at least 15 kg at baseline, the mean bedaquiline Cmax and AUC24h were similar to those of adult patients receiving the recommended adult dosage regimen. In one of these 10 pediatric patients who weighed 14 kg at baseline, the bedaquiline mean Cmax and AUC24h were 3.8-fold and 2.6-fold, respectively, higher than the mean Cmax and AUC24h in adult patients administered the recommended adult dosage regimen. The clinical significance of this higher pharmacokinetic plasma exposure in this one pediatric patient is not known.

Pediatric patients 2 years to less than 5 years of age with TB due to M. tuberculosis resistant to at least rifampin

Fifteen pediatric patients (body weight at baseline: 10 to 16 kg) received SIRTURO at a dose of 8 mg/kg once daily for 2 weeks (dose range: 80 to 120 mg; not an approved dosing regimen) followed by 4 mg/kg three times per week (dose range: 40 to 60 mg; not an approved dosing regimen) in combination with a background regimen. The results showed that the pediatric patients receiving the dosing regimens used in this pediatric study had mean bedaquiline Cmax and AUC24h comparable to those of adult patients receiving the recommended adult dosage regimen [see Use in Specific Populations (8.4)] .

The recommended dosing regimens for pediatric patients weighing 8 kg to less than 15 kg differ from those used in the pediatric clinical study. For pediatric patients weighing 8 kg to less than 15 kg, the recommended dosing regimens [see Dosage and Administration (2.4)] were determined using a pharmacokinetic modeling and simulation approach based on clinical pharmacokinetic data, to achieve exposures comparable to those observed in adults taking SIRTURO tablets [see Use in Specific Populations (8.4)] .

See Table 6for a summary of the pharmacokinetic parameters at Week 12 in pediatric patients 2 years to less than 18 years of age.

Table 6: Pharmacokinetic Parameters of Bedaquiline Following Repeat Dose Administration of SIRTURO to Pediatric Patients 2 to Less than 18 Years of Age at Week 12 Administered with Food
Pharmacokinetic Parameter | Bedaquiline Mean (SD)
 | 14 years to less than 18 years (N=15) | 5 years to less than 12 years (N=10) | 2 years to less than 5 years (N=15)
AUC24h(ng∙h/mL) | 26,300 (10,300) | 32,200 (16,300) | 26,700 (7,270) [N=10]
Cmax(ng/mL) | 1,800 (736) | 2,430 (1,670) | 1,810 (872)
Tmax(h) [Median (range)] | 4 (2 to 8) | 4 (2 to 8) | 6 (2 to 24)
Cmin(ng/mL) | 544 (263) | 461 (173) | 486 (161)
SD=Standard Deviation

Drug Interactions Studies

In vitro, bedaquiline did not significantly inhibit the activity of the following CYP450 enzymes that were tested: CYP1A2, CYP2A6, CYP2C8/9/10, CYP2C19, CYP2D6, CYP2E1, CYP3A4, CYP3A4/5 and CYP4A, and it does not induce CYP1A2, CYP2C9, CYP2C19, or CYP3A4 activities.

Bedaquiline is an in vitro substrate of CYP3A4, and because of this, the following clinical drug interaction studies were performed.

Clinical Studies

Ketoconazole:Coadministration of multiple-dose bedaquiline (400 mg once daily for 14 days) and multiple-dose ketoconazole (once daily 400 mg for 4 days) in healthy adult subjects increased the AUC24h, Cmaxand Cminof bedaquiline by 22% [90% CI (12; 32)], 9% [90% CI (-2, 21)] and 33% [90% CI (24, 43)] respectively [see Drug Interactions (7.1)and (7.3)] .

Clarithromycin:Coadministration of a single 100 mg dose of SIRTURO with clarithromycin at steady-state in healthy adults increased the mean [90% CI] bedaquiline exposure AUC240hby 14% [9%;19%].

Clofazimine:In Study 3, long-term coadministration of clofazimine and SIRTURO, as part of a combination therapy for up to 24 weeks, did not affect bedaquiline exposure.

Rifampin:In a drug interaction study of single-dose 300 mg bedaquiline and multiple-dose rifampin (once daily 600 mg for 21 days) in healthy adult subjects, the exposure (AUC) to bedaquiline was reduced by 52% [90% CI (-57; -46)] [see Drug Interactions (7.1)] .

Antimicrobial agents:The combination of multiple-dose bedaquiline 400 mg once daily with multiple-dose isoniazid/pyrazinamide (300 mg/2000 mg once daily) in healthy adult subjects did not result in clinically relevant changes in the exposure (AUC) to bedaquiline, isoniazid or pyrazinamide [see Drug Interactions (7.2)] .

In a placebo-controlled study in adult patients with, no major impact of coadministration of bedaquiline on the pharmacokinetics of ethambutol, kanamycin, pyrazinamide, ofloxacin or cycloserine was observed.

Lopinavir/ritonavir:In a drug interaction study in healthy adults of single-dose bedaquiline (400 mg) and multiple-dose lopinavir (400 mg)/ritonavir (100 mg) given twice daily for 24 days, the mean AUC of bedaquiline was increased by 22% [90% CI (11; 34)] while the mean Cmaxwas not substantially affected. In Study 4, coadministration of SIRTURO with lopinavir/ritonavir in patients coinfected with HIV increased bedaquiline exposure, with an estimated 68% [90% CI (29%; 117%)] increase in mean AUC168hat Week 24 and 72% [90% CI (32%; 123%)] at Week 40, in HIV-positive Black patients treated with lopinavir/ritonavir (N=16) compared to HIV-positive and -negative Black patients without lopinavir/ritonavir (N=67) treatment [see Drug Interactions (7.1)] .

Nevirapine:Coadministration of multiple-dose nevirapine 200 mg twice daily for 4 weeks in HIV-infected adult patients with a single 400 mg dose of bedaquiline did not result in clinically relevant changes in the exposure to bedaquiline. In Study 4, coadministration of nevirapine and SIRTURO as part of combination therapy for up to 40 weeks in patients coinfected with HIV, resulted in a 29% [90% CI (0; 50%)] decrease in bedaquiline exposure (AUC168h).

Efavirenz:Coadministration of a single dose of bedaquiline 400 mg and efavirenz 600 mg daily for 27 days to healthy adult volunteers resulted in approximately a 20% decrease in the AUCinfof bedaquiline; the Cmaxof bedaquiline was not altered. The AUC and Cmaxof the primary metabolite of bedaquiline (M2) were increased by 70% and 80%, respectively. The effect of efavirenz on the pharmacokinetics of bedaquiline and M2 following steady-state administration of bedaquiline has not been evaluated [see Drug Interactions (7.3)] .

12.4 Microbiology

Mechanism of Action

SIRTURO is a diarylquinoline antimycobacterial drug that inhibits mycobacterial ATP (adenosine 5'- triphosphate) synthase, by binding to subunit c of the enzyme that is essential for the generation of energy in M. tuberculosis.

Resistance

A potential for development of resistance to bedaquiline in M. tuberculosis exists. Modification of the atpE target gene, and/or upregulation of the MmpS5-MmpL5 efflux pump (Rv0678 mutations) have been associated with increased bedaquiline MIC values in isolates of M. tuberculosis. Target-based mutations generated in preclinical studies lead to 8- to 133-fold increases in bedaquiline MIC, resulting in MICs ranging from 0.25 to 4 micrograms per mL. Efflux-based mutations have been seen in preclinical and clinical isolates. These lead to 2- to 8-fold increases in bedaquiline MICs, resulting in bedaquiline MICs ranging from 0.25 to 0.5 micrograms per mL.

M. tuberculosis isolates that had developed at least a 4-fold increase in bedaquiline MIC were associated with mutations in Rv0678 gene that lead to upregulation of the MmpS5-MmpL5 efflux pump. Isolates with these efflux-based mutations are less susceptible to clofazimine. Isolates that are phenotypically resistant to bedaquiline should be tested for cross-resistance to clofazimine, if clofazimine is being considered as part of the treatment regimen. In Studies 2, 3 and 4 there was no clear relationship between the presence of Rv0678 mutations at baseline and treatment outcome.

Antimicrobial Activity

SIRTURO has been shown to be active in vitro and in clinical infections against most isolates of M. tuberculosis [see Indications and Usage (1)and Clinical Studies (14)] .

Susceptibility Testing

MICs for baseline M. tuberculosis isolates from patients in Studies 1 and 3 and their sputum culture conversion rates at Week 24 and from patients in the 40-week SIRTURO arm of Study 4 at Week 76 are shown in Table 7 below. Based on the available data, there was no relationship between poor microbiologic outcomes and baseline bedaquiline MIC.

Table 7: Culture Conversion Rates in SIRTURO Treatment Groups at Week 24 (Study 1 and 3) and at Week 76 (Study 4), by Baseline Bedaquiline MIC (mITT population) [7H11 agar. Patients who prematurely discontinued were categorized as culture converted (or not) based on the available data. All available data were utilized regardless of changes in treatment.]
Baseline Bedaquiline MIC (micrograms/mL) | SIRTURO Treatment Group 24-Week Culture Conversion Rate (Study 1 and Study 3) n/N (%) | SIRTURO Treatment Group 76-Week Culture Conversion Rate (Study 4, 40-Week Arm) [In addition, at Week 76 in the 40-week SIRTURO arm, there were 6 patients for whom no baseline MIC data were available. All 6 patients culture converted.] n/N (%)
Baseline Bedaquiline MIC (micrograms/mL)
≤ 0.008 | 2/2 (100) | 5/5 (100)
0.015 | 13/15 (86.7) | 26/26 (100)
0.03 | 36/46 (78.3) | 67/69 (97.1)
0.06 | 82/107 (76.6) | 51/51 (100)
0.12 | 36/42 (85.7) | 20/20 (100)
0.25 | 3/4 (75.0) | 2/2 (100)
0.5 | 5/6 (83.3) | 0
≥ 1 | 0/1 (0) | 0
N=number of patients with data per baseline BDQ MIC category; n=number of patients with culture conversion; MIC=minimum inhibitory concentration

Nineteen patients in the efficacy population of Study 3 had bedaquiline susceptibility testing results of paired (baseline and post-baseline, all of which were at Week 24 or later) genotypically identical M. tuberculosis isolates. Twelve of the 19 had a post-baseline ≥4-fold increase in bedaquiline MIC. Whole genome sequencing of nine of these 12 post-baseline isolates was done and no mutations were found in the ATP synthase operon. All nine were found to have a mutation in Rv0678. Eleven of the twelve (11/12) increases in bedaquiline MIC were seen in patients with isolates that also demonstrated increased MICs to fluoroquinolones and/or second-line injectables.

Based on available data, response rate (culture conversion at Week 120 endpoint) was similar in patients with ≥4-fold increases in bedaquiline MIC (5/12) and patients with <4-fold increases (3/7).

In the 40-week SIRTURO arm of Study 4, paired isolates (baseline and postbaseline, genotypically identical) susceptibility testing (MIC) results were available for 30 of 196 patients in the mITT population. At Week 132, three of five patients with a ≥4-fold increase in bedaquiline MIC and 25 of 25 patients with <4-fold increases had culture converted. Similarly, in the 28-week arm of Study 4, for 25 of 134 patients in the mITT population with paired isolates, two of four patients, with a ≥4-fold increase in bedaquiline MIC and 20 of 21 patients with <4-fold increases had culture converted. Based on the limited data, there was no clear relationship between bedaquiline MIC and microbiological outcomes.

For specific information regarding susceptibility test criteria and associated test methods and quality control standards recognized by FDA for this drug, please see: www.fda.gov/STIC.

13 NONCLINICAL TOXICOLOGY

13.1 Carcinogenesis, Mutagenesis, and Impairment of Fertility

Bedaquiline was not carcinogenic in rats up to the maximum tolerated dose of 10 mg/kg/day. Exposures at this dose in rats (AUCs) were within 1-fold to 2-fold of those observed in adult patients in the clinical trials.

No mutagenic or clastogenic effects were detected in the in vitro non-mammalian reverse mutation (Ames) test, in vitro mammalian (mouse lymphoma) forward mutation assay and an in vivo mouse bone marrow micronucleus assay.

SIRTURO did not affect fertility when evaluated in male and female rats at approximately twice the clinical exposure based on AUC comparisons. There was no effect of maternal treatment on sexual maturation, mating performance or fertility in F1 generation exposed to bedaquiline in utero at approximately twice the human exposure.

13.2 Animal Toxicology and/or Pharmacology

Bedaquiline is a cationic, amphiphilic drug that induced phospholipidosis (at almost all doses, even after very short exposures) in drug-treated animals, mainly in cells of the monocytic phagocytic system (MPS). All species tested showed drug-related increases in pigment-laden and/or foamy macrophages, mostly in the lymph nodes, spleen, lungs, liver, stomach, skeletal muscle, pancreas and/or uterus. After treatment ended, these findings were slowly reversible. Muscle degeneration was observed in several species at the highest doses tested. For example, the diaphragm, esophagus, quadriceps and tongue of rats were affected after 26 weeks of treatment at doses similar to clinical exposures based on AUC comparisons. These findings were not seen after a 12-week, treatment-free, recovery period and were not present in rats given the same dose biweekly. Degeneration of the fundic mucosa of the stomach, hepatocellular hypertrophy and pancreatitis were also seen.

14 CLINICAL STUDIES

14.1 SIRTURO Use in Adult Patients With Pulmonary Tuberculosis

Study 1 (NCT00449644, Stage 2) was a placebo-controlled, double-blind, randomized trial conducted in patients with newly diagnosed sputum smear-positive pulmonary TB due to M. tuberculosis resistant to at least rifampin and isoniazid. Patients were randomized to receive a combination of SIRTURO or placebo with five other antimycobacterial drugs (i.e., ethionamide, kanamycin, pyrazinamide, ofloxacin, and cycloserine/terizidone or available alternative) for a total duration of 18 to 24 months or at least 12 months after the first confirmed negative culture. Treatment was 24 weeks of treatment with SIRTURO 400 mg once daily for the first two weeks followed by 200 mg three times per week for 22 weeks or matching placebo for the same duration. Overall, 79 patients were randomized to the SIRTURO arm and 81 to the placebo arm. A final evaluation was conducted at Week 120.

Sixty-seven patients randomized to SIRTURO and 66 patients randomized to placebo had confirmed pulmonary TB due to M. tuberculosis resistant to at least rifampin and isoniazid, based on susceptibility tests (taken prior to randomization) or medical history if no susceptibility results were available, and were included in the efficacy analyses. Demographics were as follows: 64% of the study population was male, with a median age of 33 years, 38% were Black, 17% were Hispanic, 11% were White, 11% were Asian, and 24% were of another race; and 14% were HIV-positive (median CD4 cell count 446 cells/µL). Most patients had cavitation in one lung (62%); and 20% of patients had cavitation in both lungs.

Time to sputum culture conversion was defined as the interval in days between the first dose of study drug and the date of the first of two consecutive negative sputum cultures collected at least 25 days apart during treatment. In this trial, the SIRTURO treatment group had a decreased time to culture conversion and improved culture conversion rates compared to the placebo treatment group at Week 24. Median time to culture conversion was 83 days for the SIRTURO treatment group compared to 125 days for the placebo treatment group. Table 8 shows the proportion of patients with sputum culture conversion at Week 24 and Week 120.

Table 8: Culture Conversion Status and Clinical Outcome at Week 24 and Week 120 in Study 1
Microbiologic Status | SIRTURO (24 weeks) + combination of other antimycobacterial drugs N=67 | Placebo (24 weeks) + combination of other antimycobacterial drugs N=66 | Difference [95% CI] p-value
Week 24
Sputum Culture Conversion | 78% | 58% | 20.0% [4.5%, 35.6%] 0.014
Treatment failure [A patient's reason for treatment failure was counted only in the first row for which a patient qualifies.] | 22% | 42%
Died | 1% | 0%
Lack of conversion | 21% | 35%
Discontinuation | 0% | 8%
Week 120 [Patients received 24 weeks of SIRTURO or placebo for the first 24 weeks and received a combination of other antimycobacterial drugs for up to 96 weeks.]
Sputum Culture Conversion | 61% | 44% | 17.3% [0.5%, 34.0%] 0.046
Treatment failure | 39% | 56%
Died | 12% | 3%
Lack of conversion/relapse | 16% | 35%
Discontinuation | 10% | 18%

Study 2 (NCT00449644, Stage 1) was a smaller placebo-controlled study designed similarly to Study 1 except that SIRTURO or placebo was given for only eight weeks instead of 24 weeks. Patients were randomized to either SIRTURO and other drugs used to treat pulmonary TB due to M. tuberculosis resistant to at least rifampin and isoniazid (SIRTURO treatment group) (n=23) or placebo and other drugs used to treat TB (placebo treatment group) (n=24). Twenty-one patients randomized to the SIRTURO treatment group and 23 patients randomized to the placebo treatment group had confirmed pulmonary TB due to M. tuberculosis resistant to at least rifampin and isoniazid based on patients' baseline M. tuberculosis isolate obtained prior to randomization. The SIRTURO treatment group had a decreased time to culture conversion and improved culture conversion rates compared to the placebo treatment group at Week 8. At Weeks 8 and 24, the differences in culture conversion proportions were 38.9% [95% CI: (12.3%; 63.1%) and p-value: 0.004], 15.7% [95% CI: (-11.9%; 41.9%) and p-value: 0.32], respectively.

Study 3 (NCT00910871) was a Phase 2b, uncontrolled study to evaluate the safety, tolerability, and efficacy of SIRTURO as part of an individualized treatment regimen in 233 patients with sputum smear positive (within 6 months prior to screening) pulmonary TB due to M. tuberculosis resistant to at least rifampin and isoniazid, including patients with isolates resistant to second-line injectables and/or fluoroquinolones. Patients received SIRTURO for 24 weeks in combination with antimycobacterial drugs. Upon completion of the 24-week treatment with SIRTURO, all patients continued to receive their background regimen in accordance with national TB program (NTP) treatment guidelines. A final evaluation was conducted at Week 120. Treatment responses to SIRTURO at Week 120 were generally consistent with those from Study 1.

Study 4 (NCT02409290) was a Phase 3, open-label, multicenter, active-controlled, randomized trial to evaluate the efficacy and safety of SIRTURO, coadministered with other oral anti-TB drugs for 40 weeks in patients with sputum smear-positive pulmonary TB caused by M. tuberculosis that was resistant to at least rifampin. Patients in whom the M. tuberculosis strain was known to be resistant at screening to second-line injectable agents or fluoroquinolones were excluded from enrollment. When phenotypic susceptibility testing of the baseline isolates became available post-randomization, patients infected with M. tuberculosis resistant to either second-line injectable agents or fluoroquinolones were kept in the study, however, those with M. tuberculosis resistant to both second-line injectables and fluoroquinolones were discontinued from the study.

Patients were randomized to one of four treatment arms:

- Arm A (N=32), the locally used treatment in accordance with 2011 WHO treatment guidelines with a recommended 20-month duration
- Arm B (N=202), a 40-week treatment of moxifloxacin (N=140) or levofloxacin (N=62), clofazimine, ethambutol, pyrazinamide, supplemented by injectable kanamycin, high-dose isoniazid and prothionamide in the first 16 weeks (intensive phase)
- Arm C (N=211), a 40-week, all-oral treatment of SIRTURO, levofloxacin, clofazimine, ethambutol, and pyrazinamide, supplemented by high-dose isoniazid and prothionamide in the first 16 weeks (intensive phase)
- Arm D (N=143), a 28-week treatment consisting of SIRTURO, levofloxacin, clofazimine, and pyrazinamide, supplemented by kanamycin injectable and a higher isoniazid dose for the first eight weeks (intensive phase)

SIRTURO was administered 400 mg once daily for the first two weeks and 200 mg three times a week for the following 38 weeks (in Arm C) or 26 weeks (in Arm D).

All patients were to be followed up until study completion at Week 132. During study conduct, enrollment in Arms A and D was stopped due to changes in the standard of care for TB treatment. Patients already randomized to these study arms were to complete their assigned treatment and follow-up.

The primary objective was to assess whether the proportion of patients with a favorable efficacy outcome in Arm C was noninferior to that in Arm B at Week 76.

The primary efficacy outcome measure was the proportion of patients with a favorable outcome at Week 76. A favorable outcome at Week 76 was defined as the last two consecutive cultures being negative, and with no unfavorable outcome. An unfavorable outcome at Week 76 was assessed as a composite endpoint, covering both clinical and microbiological aspects such as changes in TB treatment, all-cause mortality, at least one of the last two culture results positive, or no culture results within the Week 76 window. In case of treatment failure, recurrence or serious toxicity on the allocated treatment, salvage treatment that could include SIRTURO was provided, based on investigator judgment.

The modified intent-to-treat population (mITT) was the primary efficacy population and included all randomized patients with a positive sputum culture for M. tuberculosis that was resistant to at least rifampin and not resistant to both second-line injectables and fluoroquinolones, based on susceptibility results (taken prior to randomization). A total of 196 and 187 patients were included in the mITT population in Arm C and Arm B, respectively. Overall, in both treatment arms, 62% were male of median age 33 years, 47% were Asian, 34% were Black, 19% were White, and 14% were HIV-coinfected. Most patients had lung cavitation (74%), with multiple cavities in 63% and 47% of patients in Arm C and Arm B, respectively. The baseline drug resistance profile of M. tuberculosis for Arms C and B were as follows: 14% had resistance to rifampin while susceptible to isoniazid, 75% had resistance to rifampin and isoniazid, and 10% had resistance to rifampin, isoniazid, and either a second-line injectable or a fluoroquinolone.

For efficacy analyses beyond Week 76, data collection was stopped at the point when the last recruited patient was projected to reach Week 96. The long-term efficacy data therefore include data up to at least Week 96 for all patients, and up to Week 132 for 146/196 (74.5%) patients in Arm C and 145/187 (77.5%) patients in Arm B.

Table 9 shows results for favorable and unfavorable outcomes at Week 76 and Week 132 in Study 4.

Table 9: Clinical Outcome at Week 76 and Week 132 in the mITT Population in Study 4
 | SIRTURO [Arm C 40-week, all-oral regimen of SIRTURO, levofloxacin, clofazimine, ethambutol, and pyrazinamide, supplemented by high-dose isoniazid and prothionamide in the first 16 weeks (intensive phase).] (N=196) | Active Control [Arm B 40-week control treatment of moxifloxacin or levofloxacin, clofazimine, ethambutol, pyrazinamide, supplemented by injectable kanamycin, high dose isoniazid and prothionamide in the first 16 weeks (intensive phase).] (N=187)
Favorable outcome at Week 76 n (%) | 162 (82.7) | 133 (71.1)
Difference [The adjusted difference in proportions was estimated using a stratified analysis of the risk difference from each stratum using Cochran Mantel-Haenszel weights. The analysis was stratified by randomization protocol and HIV and CD4 cell count status.] SIRTURO vs Active Control (95% CI) | 11.0% (2.9%, 19.0%)
Unfavorable outcome at Week 76 n (%) | 34 (17.3) | 54 (28.9)
Reasons for unfavorable outcome through Week 76 [Patients were classified by the first event that made the patient unfavorable. Of the patients with an unfavorable outcome at Week 76 in the control arm, 29 patients had a treatment modification from their allocated treatment that included SIRTURO as part of a salvage regimen.]
Treatment modified or extended | 16 (8.2) | 43 (23.0)
No culture results within Week 76 window | 12 (6.1) | 7 (3.7)
Death through Week 76 | 5 (2.6) | 2 (1.1)
At least one of last 2 cultures positive at Week 76 | 1 (0.5) | 2 (1.1)
Favorable outcome at Week 132 n (%) [Week 132 outcome reflects efficacy follow up until the last patient reached Week 96.] | 154 (78.6) | 129 (69.0)
Difference SIRTURO vs Active Control (95% CI) | 9.0% (0.6%,17.5%)
mITT = modified intent-to-treat

14.2 SIRTURO Use in Pediatric Patients (2 years to less than 18 years of age) With Pulmonary Tuberculosis

The pediatric trial, (NCT02354014), was designed as a single-arm, open-label, multi-cohort trial to evaluate the pharmacokinetics, safety and tolerability of SIRTURO in combination with a background regimenin patients 2 to less than 18 years of age with confirmed or probable pulmonary TB due to M. tuberculosis resistant to at least rifampin.

Pediatric Patients (12 years to less than 18 years of age)

Fifteen patients 14 years to less than 18 years of age were enrolled in the first cohort. The median age was 16 years, 80% were female, 53% were Black, 33% were White and 13% were Asian. No patient 12 years to less than 14 years of age was enrolled in this cohort. SIRTURO was administered as 400 mg once daily for the first two weeks and 200 mg three times per week for the following 22 weeks using the 100 mg tablet.

In the subset of patients with mycobacteria growth indicator tube (MGIT) culture positive pulmonary TB resistant to at least rifampin at baseline, treatment with SIRTURO resulted in conversion to a negative culture in 75% (6/8 patients) at Week 24, which was sustained at Week 120.

Pediatric Patients (5 years to less than 12 years of age)

Fifteen patients 5 years to 10 years of age were enrolled in the second cohort. The median age was seven years, 60% were female, 60% were Black, 33% were White and 7% were Asian. No patient older than 10 years to less than 12 years of age was enrolled in this cohort. The body weight range was 14 kg to 36 kg; only one patient weighing 14 kg was enrolled. SIRTURO was administered as 200 mg once daily for the first two weeks and 100 mg three times per week for the following 22 weeks using the 20 mg tablet.

In the subset of patients with MGIT culture positive pulmonary TB resistant to at least rifampin at baseline, treatment with SIRTURO resulted in conversion to a negative culture in 100% (3/3 patients) at Week 24, which was sustained at Week 120.

Pediatric Patients (2 years to less than 5 years of age)

Fifteen patients 2 years to less than 5 years of age were enrolled in the third cohort. The median age was 4 years, 47% were female, 27% were Black and 73% were Asian. At baseline, the body weight ranged from 10 kg to 16 kg. SIRTURO was administered as 8 mg/kg once daily for the first two weeks (dose range: 80 to 120 mg; not an approved dosing regimen) followed by 4 mg/kg three times per week (dose range: 40 to 60 mg; not an approved dosing regimen) for the following 22 weeks using the 20 mg tablet.

In the one patient with MGIT culture positive pulmonary TB resistant to at least rifampin at baseline, treatment with SIRTURO resulted in conversion to a negative culture (1/1 MGIT culture evaluable patient) at Week 24, which was sustained at Week 120.

16 HOW SUPPLIED/STORAGE AND HANDLING

16.1 How Supplied

SIRTURO® 20 mg tablets are supplied as uncoated white to almost white oblong functionally scored tablets with a score line on both sides, debossed with "2" and "0" on one side and plain on the other side.

SIRTURO® 100 mg tablets are supplied as uncoated white to almost white round biconvex 100 mg tablets with debossing of "T" over "207" on one side and "100" on the other side.

SIRTURO tablets are packaged in white high-density polyethylene (HDPE) bottles with child-resistant polypropylene (PP) closure with induction seal liner in the following configurations:

- 20 mg tablets – bottles of 60 tablets. Each bottle contains silica gel desiccant (NDC 59676-702-60)
- 100 mg tablets – bottles of 188 tablets (NDC 59676-701-01).

16.2 Storage and Handling

SIRTURO 20 mg Tablet

Store in original container. Bottle contains desiccant. Do not discard desiccant. Protect from light and moisture. Keep the container tightly closed.

Store at 25°C (77°F); excursions permitted between 15°C to 30°C (59°F to 86°F) [see USP Controlled Room Temperature].

SIRTURO 100 mg Tablet

Dispense in original container. Store tablets dispensed outside the original container in a tight light-resistant container with an expiration date not to exceed 3 months. Protect from light. Keep the container tightly closed.

Store at 25°C (77°F); excursions permitted from 15°C to 30°C (59°F to 86°F) [see USP Controlled Room Temperature].

17 PATIENT COUNSELING INFORMATION

Advise patients to read the FDA-approved patient labeling (Medication Guide).

Serious Adverse Reactions

Advise patients that the following serious side effects can occur with SIRTURO: heart rhythm abnormalities, death and/or hepatitis. In addition, advise patients about other potential side effects: nausea, vomiting, joint pain, increased transaminases, dizziness, headache, myalgia, diarrhea, increased blood amylase, hemoptysis, chest pain, anorexia, rash, and/or abdominal pain. Additional testing may be needed to monitor or reduce the likelihood of adverse effects.

Compliance with Treatment

Advise patients to take SIRTURO in combination with other antimycobacterial drugs as prescribed. Emphasize compliance with the full course of therapy. Advise patients that skipping doses or not completing the full course of therapy may (1) decrease the effectiveness of the treatment and (2) increase the likelihood that their mycobacterium may develop resistance and the disease will not be treatable by SIRTURO or other antimycobacterial drugs in the future.

If a dose is missed during the first 2 weeks of treatment, advise patients not to make up the missed dose but to continue the usual dosing schedule. From Week 3 onwards, if a dose is missed, advise patients to take the missed dose as soon as possible, and then resume the 3 times a week regimen.

Ensure that the total dose of SIRTURO during a 7-day period does not exceed the recommended weekly dose (with at least 24 hours between each intake).

Administration Instructions

Advise patients to take SIRTURO with food.

Advise patients who have difficulty swallowing tablets that SIRTURO 20 mg tablet can be administered by the following methods:

- Dispersed in water and the mixture administered immediately. To aid with administration, the dispersed mixture in water can be further mixed with a beverage (e.g., water, milk products, apple juice, orange juice, cranberry juice or carbonated beverage) or soft food (e.g., yogurt, apple sauce, mashed banana or porridge) and then administered immediately,
- Crushed and mixed with soft food and the mixture administered immediately,
- Administered through a feeding tube [see Dosage and Administration (2.6)] .

Use with Alcohol and other Medications

Instruct patients to abstain from alcohol, hepatotoxic medications or herbal products.

Advise patients to discuss with their physician the other medications they are taking and other medical conditions before starting treatment with SIRTURO.

Lactation

Advise patients not to breastfeed during treatment with SIRTURO and for 27.5 months after the last dose unless infant formula is not available. If an infant is exposed to bedaquiline through breast milk, advise caregivers to monitor the infant for signs of bedaquiline-related adverse reactions, such as hepatotoxicity (yellowing of the eyes and changes in the color of the urine or stool) [see Adverse Reactions (6)and Use in Specific Populations (8.2)] .

Manufactured for:
Janssen Products, LP
Horsham, PA 19044, USA

For patent information: www.janssenpatents.com
©Johnson & Johnson and its affiliates 2012-2025

MEDICATION GUIDE
SIRTURO® (ser toor' oh)
(bedaquiline)
tablets, for oral use

Read this Medication Guide before you start taking SIRTURO and each time you get a refill. There may be new information. This information does not take the place of talking with your healthcare provider about your medical condition or your treatment.

What is the most important information I should know about SIRTURO?

SIRTURO can cause serious side effects, including:
A serious heart rhythm problem called QTc prolongation. This condition can cause an abnormal heartbeat in people who take SIRTURO. Your healthcare provider should check your heart and do blood tests before and during treament with SIRTURO. Tell your healthcare provider right away if you have a change in your heartbeat (a fast or irregular heartbeat) or if you feel dizzy or faint.

What is SIRTURO?
SIRTURO is a diarylquinoline antibiotic prescription medicine used as a part of combination therapy in adults and children (2 years of age and older and weighing at least 17.6 pounds) with pulmonary tuberculosis (TB) of the lungs that is resistant to at least rifampin and isoniazid.
It is not known if SIRTURO is safe and effective in:

- people who have a tuberculosis (TB) infection, but do not show symptoms of TB (also known as latent TB).
- people who have TB of the lungs that is not resistant to antibiotics.
- people who have types of TB other than TB of the lungs.
- people who have an infection caused by bacteria other than TB.
- children under 2 years of age or weighing less than 17.6 pounds (8 kg).

Before you take SIRTURO, tell your healthcare provider about all your medical conditions including, if you:

- take any medicines for your heart.
- have had an abnormal heart rhythm (ECG) or other heart problems.
- have a family history of a heart problem called "congenital long QTc syndrome" or heart failure.
- have decreased thyroid gland function (hypothyroidism).
- have liver or kidney problems.
- have HIV infection.
- are pregnant or plan to become pregnant. It is not known if SIRTURO will harm your unborn baby.
- are breastfeeding or plan to breastfeed. Do not breastfeed while taking SIRTURO, and for 27.5 months (2 years 3 months and 2 weeks) after your last dose, unless formula is not available. SIRTURO passes into breast milk. Talk to your healthcare provider about the best way to feed your baby while taking SIRTURO.
  - If you have to breastfeed because formula is not available, tell your healthcare provider right away if your baby has:

- yellowing of their eyes.
- darker than usual urine color.

- lighter than usual stool color or stool that is pale or light brown.

Tell your healthcare provider about all the medicines you take, including prescription and over-the-counter medicines, vitamins, and herbal supplements.
You should not take certain liver medicines or herbal supplements while taking SIRTURO.

How should I take SIRTURO?

- Take SIRTURO exactly as your healthcare provider tells you to take it.
- You will take SIRTURO for a total of 24 weeks. You may need to take your other TB medicines for longer than 24 weeks. If you are not sure, you should talk with your healthcare provider.
- SIRTURO must always be taken with other medicines to treat TB. Your healthcare provider will decide which other medicines you should take with SIRTURO.
- It is important that you complete the full course of treatment with SIRTURO and not skip doses. Skipping doses may decrease the effectiveness of the treatment and increase the chances that your TB will not be treatable by SIRTURO or other medicines.

Week 1 and Week 2:
Take your prescribed dose 1 time each day.
Week 3 to Week 24:

- Take your prescribed dose 3 times a week.
- Take SIRTURO doses at least 48 hours apart. For example, you may take SIRTURO on Monday, Wednesday and Friday every week from week 3 to week 24.
- Do not skip SIRTURO doses. If you skip doses, or do not complete the total 24 weeks of SIRTURO, your treatment may not work as well, and your TB may be harder to treat.
- If you take more SIRTURO than you should, talk to a healthcare provider right away.

If you miss your SIRTURO dose during Week 1 or Week 2:

- Do not take a double dose to make up for the missed dose. Take the next dose as usual.

If you miss your SIRTURO dose during Week 3 to Week 24:

- Take the missed dose as soon as possible and continue taking SIRTURO on the 3 times a week schedule.
- Make sure that there is at least 24 hours between taking the missed dose and the next scheduled dose.
- Do not take more than the prescribed weekly dose in a 7-day period.
- If you miss a dose and you are not sure what to do, talk to your healthcare provider.

- Do not stop taking SIRTURO without first talking to your healthcare provider.

SIRTURO 20 mg tablet

- Always take SIRTURO with food.
  - Can swallow whole tablets:
    - Swallow tablets whole with water or
    - Split tablets in half at the score line in the middle of the tablet into 2 equal parts of 10 mg each, then swallow both half parts of SIRTURO with water.
  - Cannot swallow whole tablets:
    - Use 1 teaspoon (5 mL) of water for a maximum of 5 SIRTURO tablets. Mix well in a drinking cup.
      - Swallow mixture immediately, or
      - To help with taking SIRTURO you may add at least 1 more teaspoon (5 mL) of beverage or soft food and mix. Beverages such as water, milk products, apple juice, orange juice, cranberry juice or carbonated beverages may be used. Soft foods such as yogurt, apple sauce, mashed banana or porridge may be used.
      - Swallow mixture immediately.
      - Make sure no remaining medicine is left in the drinking cup, rinse with beverage or soft food and swallow mixture immediately.
      - If you need more than 5 tablets of SIRTURO to get your total dose, repeat the steps above until you reach your prescribed dose.
        or
    - Crush tablets and mix with soft food. Soft food such as yogurt, apple sauce, mashed bananas or porridge may be used. Swallow mixture immediately. Make sure no remaining medicine is left in the container, add more soft food and swallow mixture immediately.
  - SIRTURO 20 mg tablets may also be given through certain feeding tubes by your healthcare provider.

SIRTURO 100 mg tablet

- Always take SIRTURO with food. Swallow tablets whole with water.

What should I avoid while taking SIRTURO?

- You should not drink alcohol while taking SIRTURO.

What are the possible side effects of SIRTURO?
SIRTURO may cause serious side effects, including:

- See " What is the most important information I should know about SIRTURO?"
- liver problems (hepatotoxicity). Your healthcare provider should do blood tests to check your liver before you start taking SIRTURO and during treatment. Call your healthcare provider right away if you have unexplained symptoms such as:

- nausea or vomiting
- fever
- itching
- loss of appetite
- dark colored urine

- stomach pain
- weakness
- unusual tiredness
- light colored bowel movements
- yellowing of your skin or the white of your eyes

The most common side effects of SIRTURO in adults include:

- heart rhythm problem (QTc prolongation)

- nausea

- vomiting

- joint pain

- rash

- increased liver enzymes

- stomach pain

- itching

- dizziness

- headache

- chest pain

- trouble sleeping

- dry skin

- heart pounding

- coughing up blood

The most common side effects of SIRTURO in children 12 years to less than 18 years of age include joint pain, nausea and stomach pain.
The most common side effect of SIRTURO in children 5 years to less than 12 years of age is increased level of liver enzymes in the blood.
The most common side effect of SIRTURO in children 2 years to less than 5 years of age is vomiting.
These are not all the possible side effects of SIRTURO. For more information, ask your healthcare provider or pharmacist.
Call your doctor for medical advice about side effects. You may report side effects to FDA at 1-800-FDA-1088.

How should I store SIRTURO?

- Store SIRTURO at room temperature between 68°F to 77°F (20°C to 25°C).
- Keep SIRTURO in the original container.
- Protect SIRTURO from light.
- The SIRTURO 20 mg container contains a desiccant packet to keep your medicine dry (protect it from moisture). Do not throw away (discard) the desiccant.

Keep SIRTURO and all medicines out of reach of children.

General information about the safe and effective use of SIRTURO:
This Medication Guide summarizes the most important information about SIRTURO. If you would like more information, talk to your healthcare provider. You can ask your pharmacist or healthcare provider for information about SIRTURO that is written for health professionals.

What are the ingredients in SIRTURO?
Active ingredient: bedaquiline fumarate
SIRTURO 20 mg tablets contain the following inactive ingredients: colloidal silicon dioxide, crospovidone, hypromellose 2910 5 mPa.s, polysorbate 20, purified water (removed during processing), silicified microcrystalline cellulose and sodium stearyl fumarate.
SIRTURO 100 mg tablets contain the following inactive ingredients: colloidal silicon dioxide, corn starch, croscarmellose sodium, hypromellose 2910 15 mPa.s, lactose monohydrate, magnesium stearate, microcrystalline cellulose, polysorbate 20, purified water (removed during processing).
Manufactured for: Janssen Products, LP, Horsham, PA 19044, USA
For patent information: www.janssenpatents.com
© Johnson & Johnson and its affiliates 2012-2025

This Medication Guide has been approved by the U.S. Food and Drug Administration

Revised: 7/2025

PRINCIPAL DISPLAY PANEL - 20 mg Tablet Bottle Label

NDC 59676-702-60

Sirturo®
(bedaquiline) Tablets

20 mg

ATTENTION: Dispense the enclosed
Medication Guide to each patient.

Each tablet contains 20 mg of bedaquiline
(equivalent to 24.18 mg of bedaquiline fumarate).

Rx only
60 Tablets

Johnson

&Johnson

PRINCIPAL DISPLAY PANEL - 100 mg Tablet Bottle Label

NDC 59676-701-01

Sirturo®
(bedaquiline) tablets

100 mg

Attention: Dispense the enclosed

Medication Guide to each patient.

Each tablet contains 100 mg of

bedaquiline (equivalent to

120.89 mg of bedaquiline fumarate).

Rx only
188 Tablets

Johnson

&Johnson